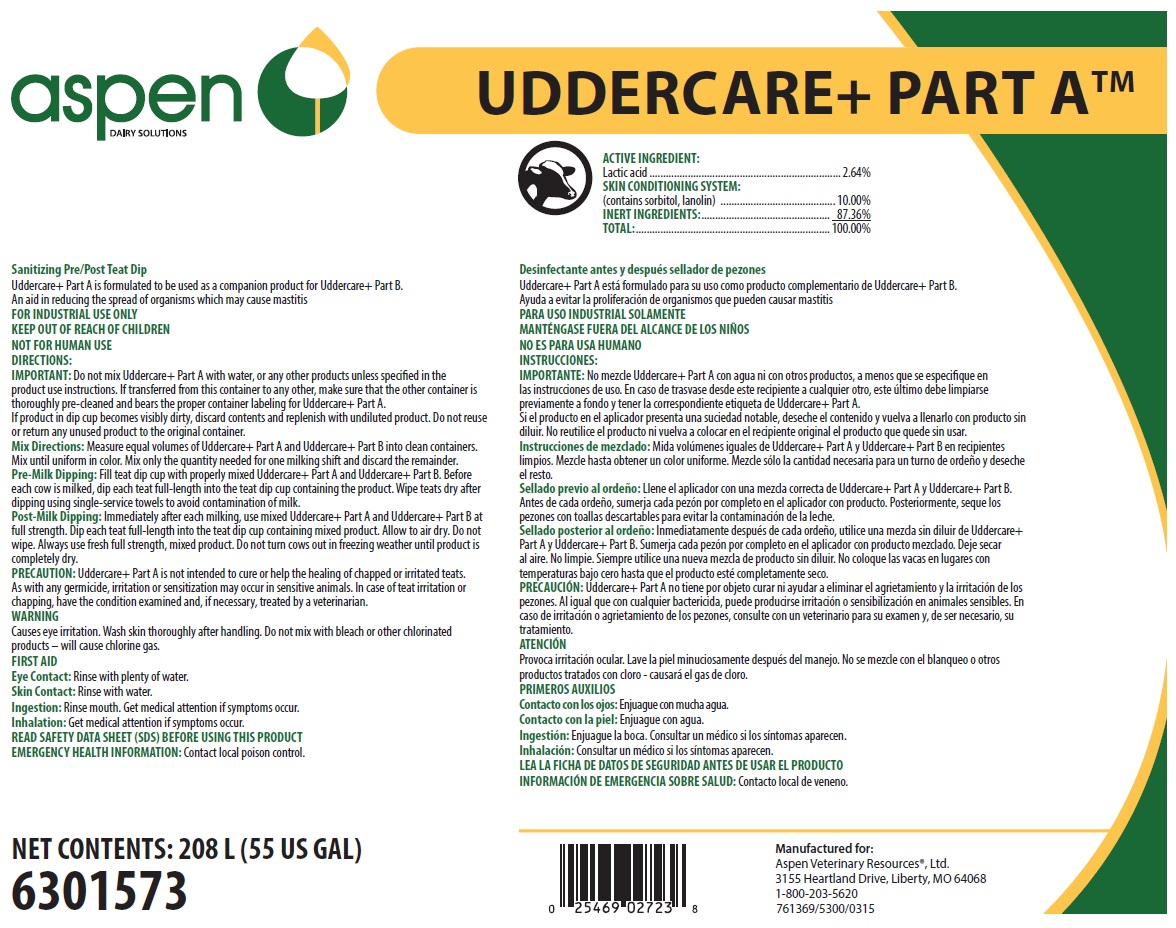 DRUG LABEL: Uddercare Plus Part A
NDC: 46066-406 | Form: SOLUTION
Manufacturer: Aspen Veterinary Resources, Ltd.
Category: animal | Type: OTC ANIMAL DRUG LABEL
Date: 20250626

ACTIVE INGREDIENTS: LACTIC ACID 26.4 mg/1 mL
INACTIVE INGREDIENTS: SORBITOL; LANOLIN; WATER

SAFE HANDLING WARNING

FOR INDUSTRIAL USE ONLY

KEEP OUT OF REACH OF CHILDREN

NOT FOR HUMAN USE

WARNING

Causes eye irritation. Wash skin thoroughly after handling. Do not mix with bleach or other chlorinated products – will cause chlorine gas.

DIRECTIONS:

IMPORTANT: Do not mix Uddercare+ Part A with water, or any other products unless specified in the product use instructions. If transferred from this container to any other, make sure that the other container is thoroughly pre-cleaned and bears the proper container labeling for Uddercare+ Part A.

If product in dip cup becomes visibly dirty, discard contents and replenish with undiluted product. Do not reuse or return any unused product to the original container.

Mix Directions: Measure equal volumes of Uddercare+ Part A and Uddercare+ Part B into clean containers. Mix until uniform in color. Mix only the quantity needed for one milking shift and discard the remainder.

Pre-Milk Dipping: Fill teat dip cup with properly mixed Uddercare+ Part A and Uddercare+ Part B. Before each cow is milked, dip each teat full-length into the teat dip cup containing the product. Wipe teats dry after dipping using single-service towels to avoid contamination of milk.

Post-Milk Dipping: Immediately after each milking, use mixed Uddercare+ Part A and Uddercare+ Part B at full strength. Dip each teat full-length into the teat dip cup containing mixed product. Allow to air dry. Do not wipe. Always use fresh full strength, mixed product. Do not turn cows out in freezing weather until product is completely dry.

PRECAUTION: Uddercare+ Part A is not intended to cure or help the healing of chapped or irritated teats. As with any germicide, irritation or sensitization may occur in sensitive animals. In case of teat irritation or chapping, have the condition examined and, if necessary, treated by a veterinarian.

OTHER SAFETY INFORMATION

FIRST AID

Eye Contact: Rinse with plenty of water.

Skin Contact: Rinse with water.

Ingestion: Rinse mouth. Get medical attention if symptoms occur.

Inhalation: Get medical attention if symptoms occur.

READ SAFETY DATA SHEET (SDS) BEFORE USING THIS PRODUCT

EMERGENCY HEALTH INFORMATION: Contact local poison control.

Representative label and principal display panel

aspen DAIRY SOLUTIONS

UDDERCARE+ PART A™

ACTIVE INGREDIENT:

Lactic acid....................................................................... 2.64%

SKIN CONDITIONING SYSTEM:

(contains sorbitol, lanolin) ........................................... 10.00%

INERT INGREDIENTS:................................................ 87.36%

TOTAL:........................................................................ 100.00%

Sanitizing Pre/Post Teat Dip

Uddercare+ Part A is formulated to be used as a companion product for Uddercare+ Part B.

An aid in reducing the spread of organisms which may cause mastitis

NET CONTENTS: 208 L (55 US GAL)

6301573

Manufactured for:

Aspen Veterinary Resources®, Ltd.

3155 Heartland Drive, Liberty, MO 64068

1-800-203-5620

761369/5300/0315